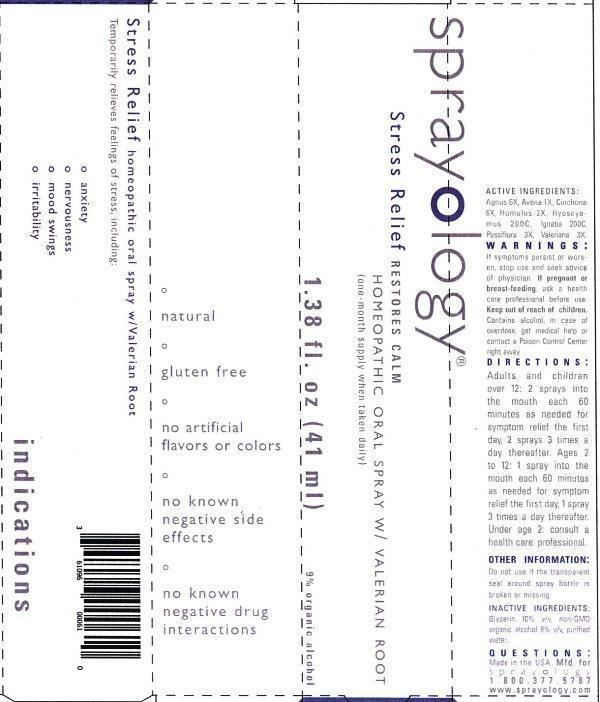 DRUG LABEL: Sprayology Stress Relief
NDC: 61096-0006 | Form: LIQUID
Manufacturer: Eight and Company
Category: homeopathic | Type: HUMAN OTC DRUG LABEL
Date: 20140226

ACTIVE INGREDIENTS: CHASTE TREE 6 [hp_X]/41 mL; AVENA SATIVA FLOWERING TOP 1 [hp_X]/41 mL; CINCHONA OFFICINALIS BARK 6 [hp_X]/41 mL; HOPS 2 [hp_X]/41 mL; HYOSCYAMUS NIGER 200 [hp_C]/41 mL; STRYCHNOS IGNATII SEED 200 [hp_C]/41 mL; PASSIFLORA INCARNATA FLOWERING TOP 3 [hp_X]/41 mL; VALERIAN 3 [hp_X]/41 mL
INACTIVE INGREDIENTS: GLYCERIN; ALCOHOL; WATER

Sprayology Stress Relief

ACTIVE INGREDIENT

Active Ingredients: Agnus castus 6X, Avena sativa 1X, Cinchona officinalis 6X, Humulus lupulus 2X, Hyoscyamus niger 200C, Ignatia amara 200C, Passiflora incarnata 3X, Valeriana officinalis 3X

WARNINGS

Warnings: If symptoms persist or worsen, stop use and seek advice of physician. If pregnant or breast-feeding, ask a health care professional before use. Keep out of reach of children. Contains alcohol, in case of overdose, get medical help or contact a Poison Control Center right away.

Keep out of reach of children.

Directions:

- Adults and children over 12: 2 sprays into the mouth each 60 minutes as needed for symptom relief the first day, 2 sprays 3 times a day thereafter.
- Ages 2 to 12: 1 spray into the mouth each 60 minutes as needed for symptom relief the first day, 1 spray 3 times a day thereafter.
- Under age 2: consult a health care professional.

PURPOSE

Temporarily relieves feelings of stress, including:

- anxiety
- nervousness
- mood swings
- irritability

Other Information: Do not use if the transparent seal around spray bottle is broken or missing.

INACTIVE INGREDIENT

Inactive Ingredients: Glycerin 10% v/v, non-GMO organic alcohol 9% v/v and purified water.

INDICATIONS AND USAGE

Temporarily relieves feelings of stress, including:

° anxiety

° nervousness

° mood swings

° irritability

° natural

° gluten free

° no artificial flavors or colors

° no known negative side effects

° no known negative drug interactions